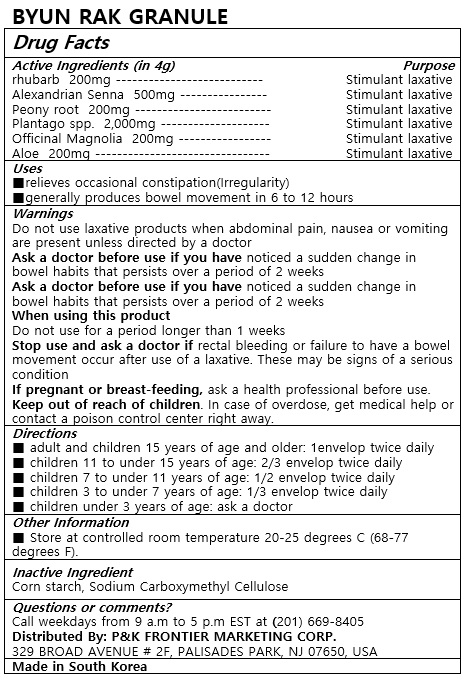 DRUG LABEL: BYUN RAK
NDC: 72689-0043 | Form: GRANULE
Manufacturer: OASIS TRADING
Category: otc | Type: HUMAN OTC DRUG LABEL
Date: 20190321

ACTIVE INGREDIENTS: SENNA LEAF 500 mg/4 g; ALOE 200 mg/4 g; MAGNOLIA OFFICINALIS BARK 200 mg/4 g; PAEONIA LACTIFLORA ROOT 200 mg/4 g; RHUBARB 200 mg/4 g; PLANTAGO INDICA SEED COAT 2000 mg/4 g
INACTIVE INGREDIENTS: CARBOXYMETHYLCELLULOSE SODIUM; STARCH, CORN

ACTIVE INGREDIENT

rhubarb ....................... 200mg
Alexandrian Senna ............................. 500mg
Peony root ......................... 200mg
Plantago spp. .........................2000mg
Officinal Magnolia .......... 200mg
Aloe ......................... 200mg

PURPOSE

■relieves occasional constipation(Irregularity)
■generally produces bowel movement in 6 to 12 hours

Keep out of reach of children

INDICATIONS AND USAGE

■ adult and children 15 years of age and older: 1envelop twice daily
■ children 11 to under 15 years of age: 2/3 envelop twice daily
■ children 7 to under 11 years of age: 1/2 envelop twice daily
■ children 3 to under 7 years of age: 1/3 envelop twice daily
■ children under 3 years of age: ask a doctor

Do not use laxative products when abdominal pain, nausea or vomiting are present unless directed by a doctor
Ask a doctor before use if you have noticed a sudden change in bowel habits that persists over a period of 2 weeks
Ask a doctor before use if you have noticed a sudden change in bowel habits that persists over a period of 2 weeks
When using this product
Do not use for a period longer than 1 weeks
Stop use and ask a doctor if rectal bleeding or failure to have a bowel movement occur after use of a laxative. These may be signs of a serious condition
If pregnant or breast-feeding, ask a health professional before use.
keep out of reach of children. In case of overdose, get medical help or contact a poison contral center right away.

INACTIVE INGREDIENT

corn starch, Sodium Carboxymethyl Cellulose

DOSAGE AND ADMINISTRATION

For oral use only